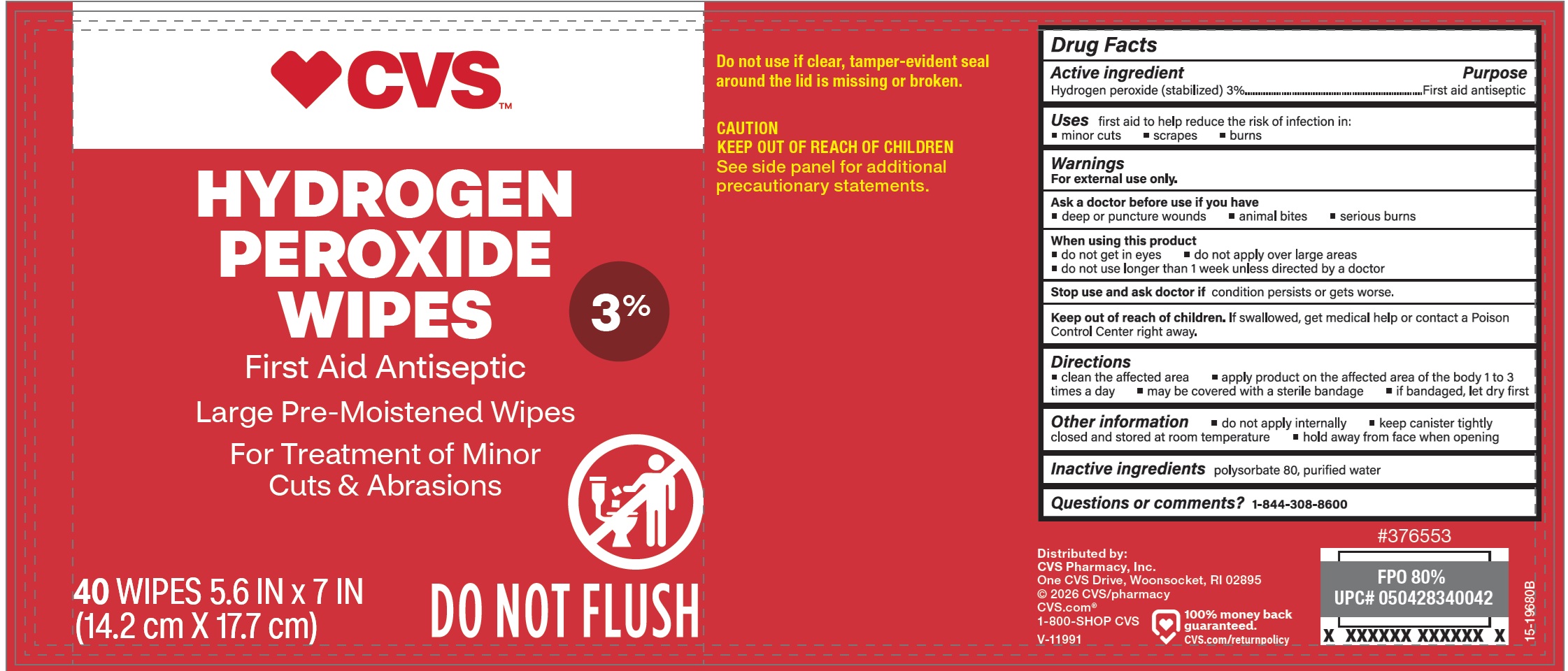 DRUG LABEL: CVS Hydrogen Peroxide Wipes
NDC: 51316-950 | Form: CLOTH
Manufacturer: CVS Pharmacy
Category: otc | Type: HUMAN OTC DRUG LABEL
Date: 20260120

ACTIVE INGREDIENTS: HYDROGEN PEROXIDE 30 mg/1 g
INACTIVE INGREDIENTS: POLYSORBATE 80; WATER

CVS Hydrogen Peroxide Wipes

Active ingredient

Hydrogen Peroxide(stabilized)3%

Purpose

First aid antiseptic

Uses

first aid to help reduce the risk of infection in:

• minor cuts • scrapes • burns

Warnings

For external use only.

Ask a doctor before use if you have

• deep or puncture wounds • animal bites • serious burns

When using this product

• do not get in eyes • do not apply over large areas • do not use longer than 1 week unless directed by a doctor

Stop use and ask doctor if

condition persists or gets worse.

Keep out of reach of children.

If swallowed, get medical help or contact a poison control Center right away.

Directions

• clean the affected area • apply product on the affected area of the body 1 to 3 times a day • may be covered with a sterile bandage • if bandaged, let dry first

Other information

• do not apply internally • keep canister tightly closed and stored at room temperature • hold away from face when opening

Inactive ingredients

polysorabate 80, purified water

Questions or comments?

1-844-308-8600